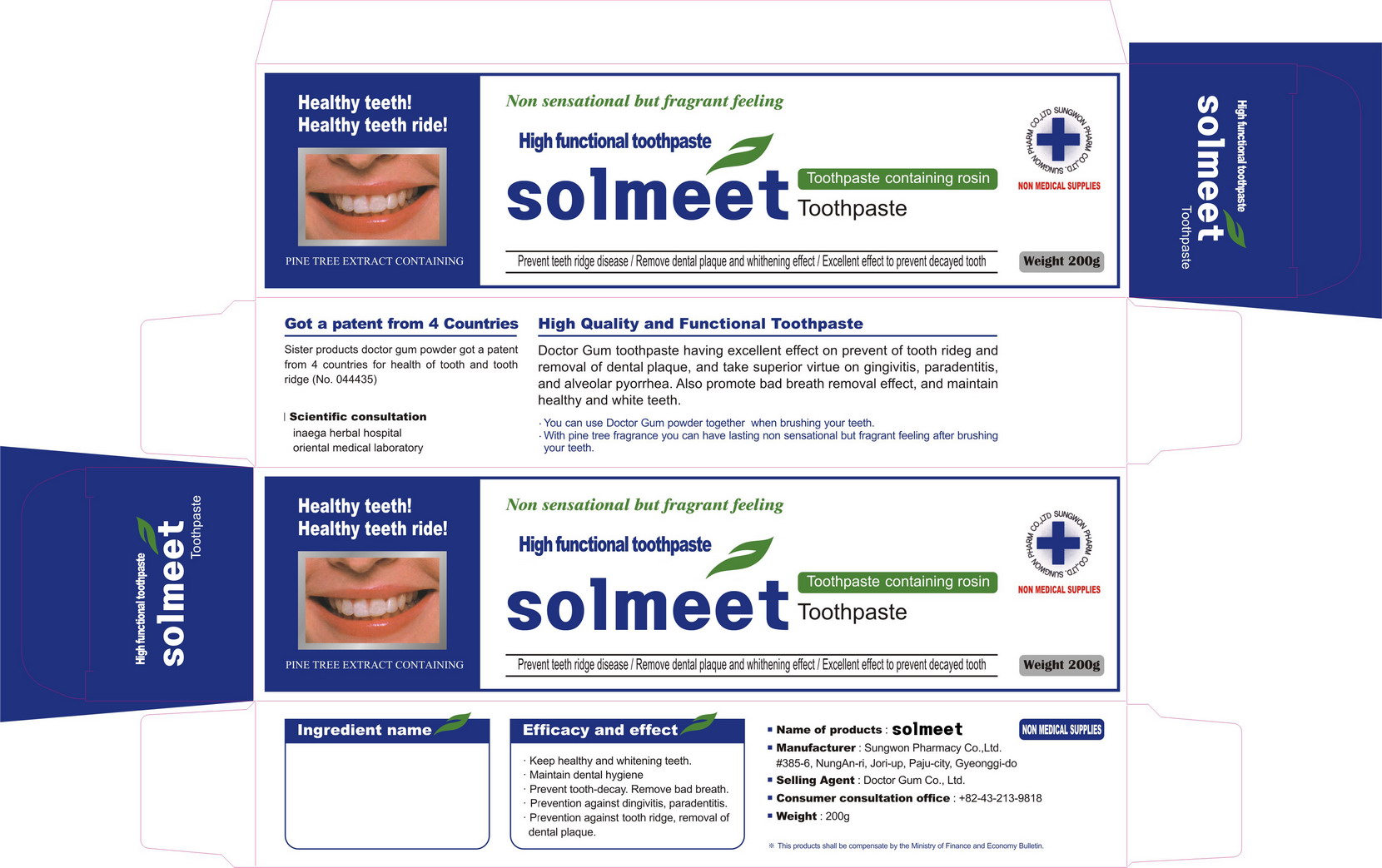 DRUG LABEL: Solmeet
NDC: 42352-7001 | Form: PASTE, DENTIFRICE
Manufacturer: Solbin Co., Ltd
Category: otc | Type: HUMAN OTC DRUG LABEL
Date: 20101222

ACTIVE INGREDIENTS: CALCIUM CARBONATE 15.85 g/100 g; DIBASIC CALCIUM PHOSPHATE DIHYDRATE 0.6 g/100 g; AMINOCAPROIC ACID 0.05 g/100 g; ALCLOXA 0.05 g/100 g
INACTIVE INGREDIENTS: SODIUM CHLORIDE; GLYCERIN; SORBITOL; POLYETHYLENE GLYCOL 1500; CARBOXYMETHYLCELLULOSE SODIUM; SODIUM LAURYL SULFATE; METHYLPARABEN; XYLITOL; LEVOMENTHOL; PEPPERMINT; FD&C YELLOW NO. 5; FD&C BLUE NO. 1; ANGELICA DAHURICA ROOT; PHELLODENDRON AMURENSE BARK; ROSIN; WATER

Drug Facts

Active Ingredient: Calcium Carbonate, Dibasic Calcium Phosphate Hydrate, Aminocarproic Acid, Aluminium Chlorohydroxy Allantoinate

INACTIVE INGREDIENT

Inactive ingredients: calcium carbonate, dibasic calcium phosphate hydrate, amonicaproic acid, aluminium chlorohydroxy allantoinate, glycerine, D-sorbitol, polyethylene glycol-1500, carboxymethylcellulose sodium, sodium lauryl sulfate, methylparaben, xylitol, L-menthol, peppermint oil, yellow no.5, blue no.1, angelica dahurica root extract, phellodendron bark extract, rosin, purified water

PURPOSE

for dental care

keep out of reach of the children

INDICATIONS AND USAGE

use when is needed

WARNINGS

- do not swallow when using this product
- if more than used for rinsing is accidentally swallowed, get medical helps or contact a poison control center right away

DOSAGE AND ADMINISTRATION

apply proper amount on your toothbrush